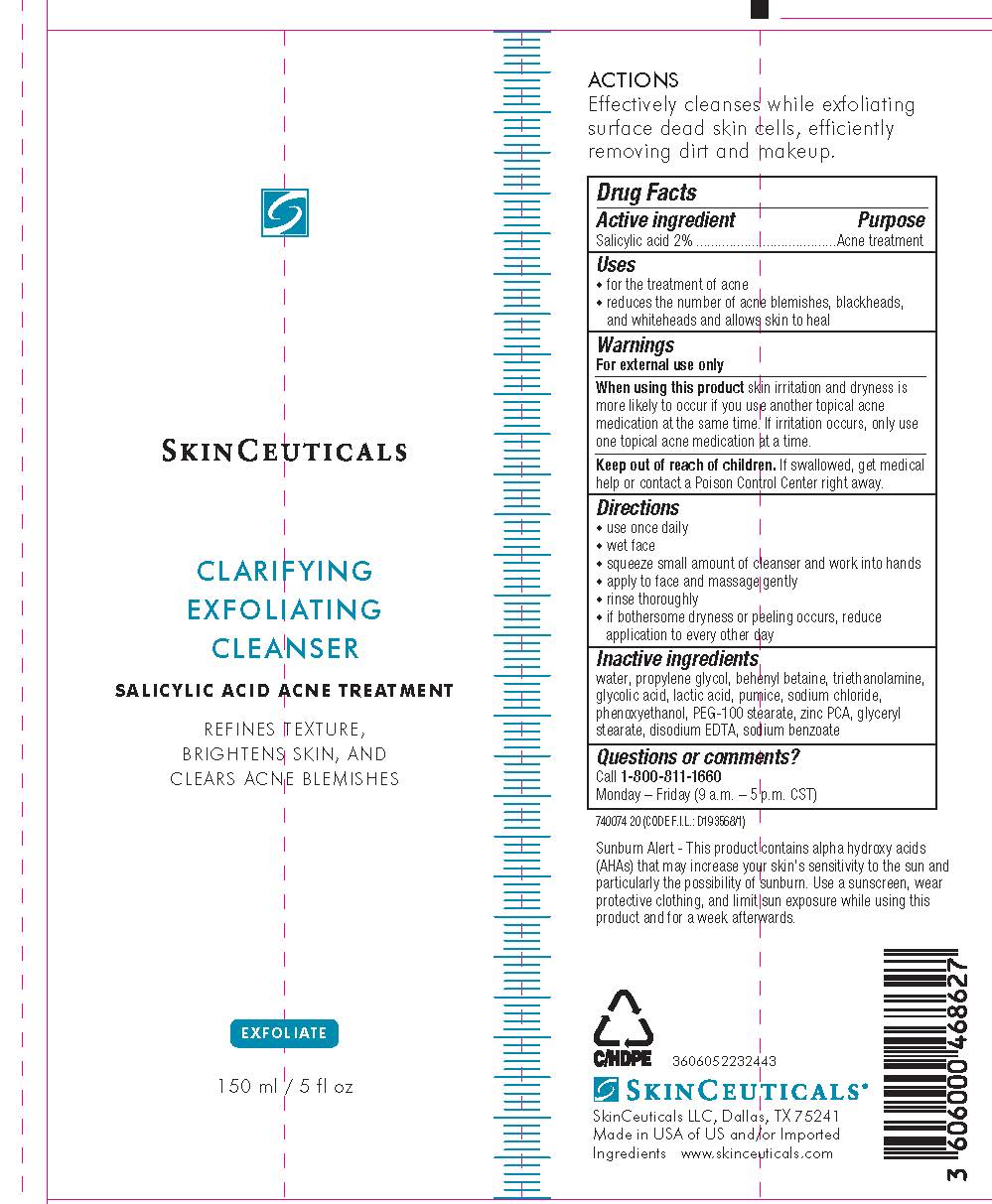 DRUG LABEL: SkinCeuticals Clarifying Exfoliating Cleanser
NDC: 49967-468 | Form: CREAM
Manufacturer: L'Oreal USA Products Inc
Category: otc | Type: HUMAN OTC DRUG LABEL
Date: 20241227

ACTIVE INGREDIENTS: SALICYLIC ACID 20 mg/1 mL
INACTIVE INGREDIENTS: WATER; PROPYLENE GLYCOL; BEHENYL BETAINE; TROLAMINE; GLYCOLIC ACID; LACTIC ACID; PUMICE; SODIUM CHLORIDE; PHENOXYETHANOL; PEG-10 STEARATE; ZINC PIDOLATE; GLYCERYL MONOSTEARATE; EDETATE DISODIUM; SODIUM BENZOATE

Drug Facts

Active ingredient

Salicylic acid 2%

Purpose

Acne treatment

Uses

- for the treatment of acne
- reduces the number of acne blemishes, blackheads, and whiteheads and allows skin to heal

Warnings

For external use only

When using this product

skin irritation and dryness is more likely to occur if you use another topical acne medication at the same time. If irritation occurs, only use one topical acne medication at a time.

Keep out of reach of children.

If swallowed, get medical help or contact a Poison Control Center right away.

Directions

- use once daily
- wet face
- squeeze small amount of cleanser and work into hands
- apply to face and massage gently
- rinse thoroughly
- if bothersome drying or peeling occurs, reduce application to every other day

Inactive ingredients

water, propylene glycol, behenyl betaine, triethanolamine, glycolic acid, lactic acid, pumice, sodium chloride, phenoxyethanol, PEG-100 sterarate, zinc PCA, glyceryl stearate, disodium EDTA, sodium benzoate

Questions?

Call 800-811-1660

Monday - Friday (9 a.m. - 5 p.m. CST)